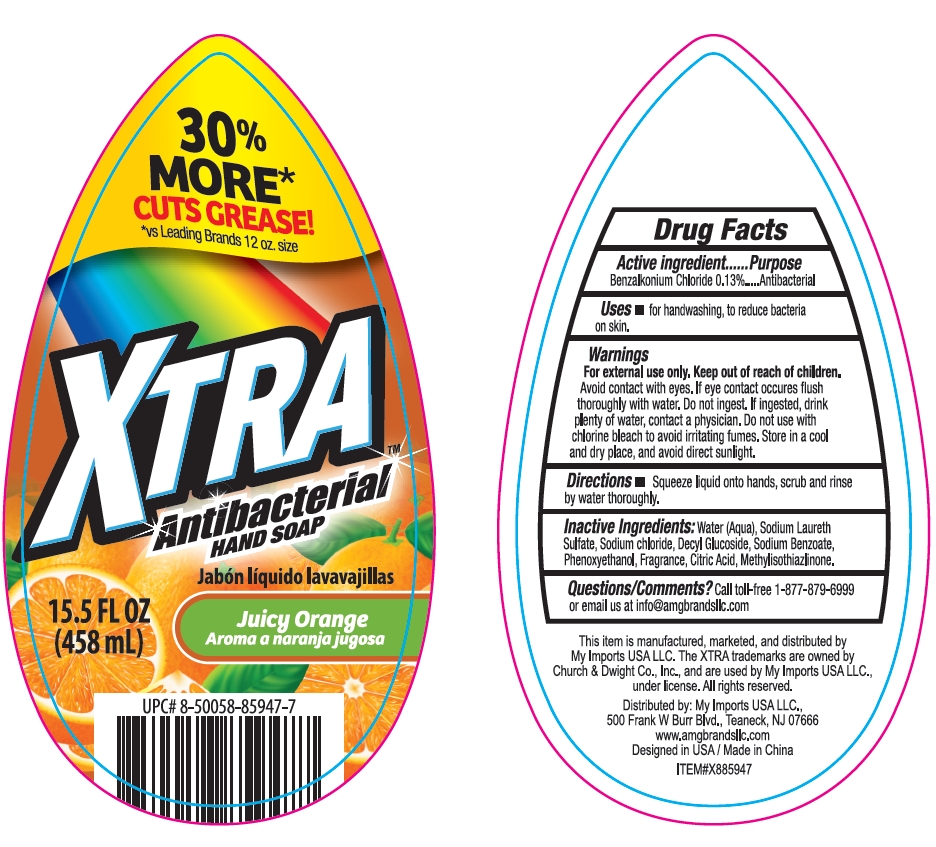 DRUG LABEL: XTRA Squeeze Antibacterial Hand Juicy Orange
NDC: 51628-4442 | Form: GEL
Manufacturer: MY IMPORTS USA LLC
Category: otc | Type: HUMAN OTC DRUG LABEL
Date: 20250319

ACTIVE INGREDIENTS: BENZALKONIUM CHLORIDE 0.13 g/100 mL
INACTIVE INGREDIENTS: SODIUM LAURETH SULFATE; PHENOXYETHANOL; DECYL GLUCOSIDE; CITRIC ACID; METHYLISOTHIAZOLINONE; SODIUM BENZOATE; WATER; SODIUM CHLORIDE

XTRA Squeeze Antibacterial Hand Soap Juicy Orange

Active ingredient

Benzalkonium Chloride 0.13%

Purpose

Antibacterial Hand Soap

Uses

for handwashing, to reduce bacteria on skin

Warnings

For external use only.

Keep out of reach of children

Do not use with chlorine bleach to avoid irritating fumes. Store in a cool and dry place, and avoid direct sunlight.

Avoid contact with eyes.

If eye contact occures fush thoroughly with water.

Do not ingest. If ingested, drink plenty of water, contact a physician.

STORAGE AND HANDLING

Store in a cool and dry pleace, and avoid direct sunlight.

Directions

Squeeze liquid onto hands, scrub and rinse by water thoroughly.

Inactive ingredients

Water (Aqua）

Sodium Laureth Sulfate

Decyl Glucoside

Citric Acid

Methylisothiazlione

Phenoxyethanol

Sodium Benzoate

Fragrance